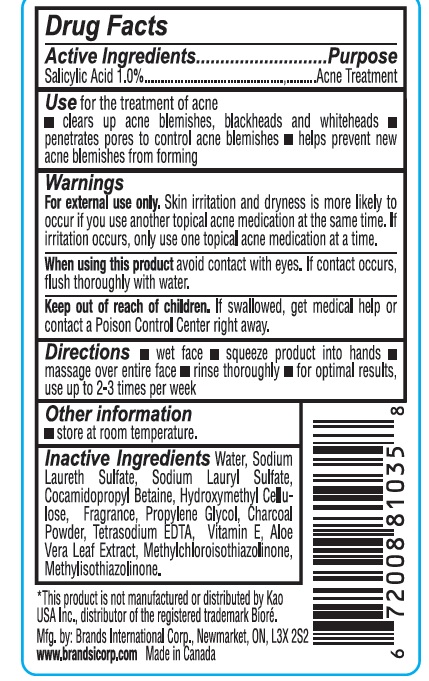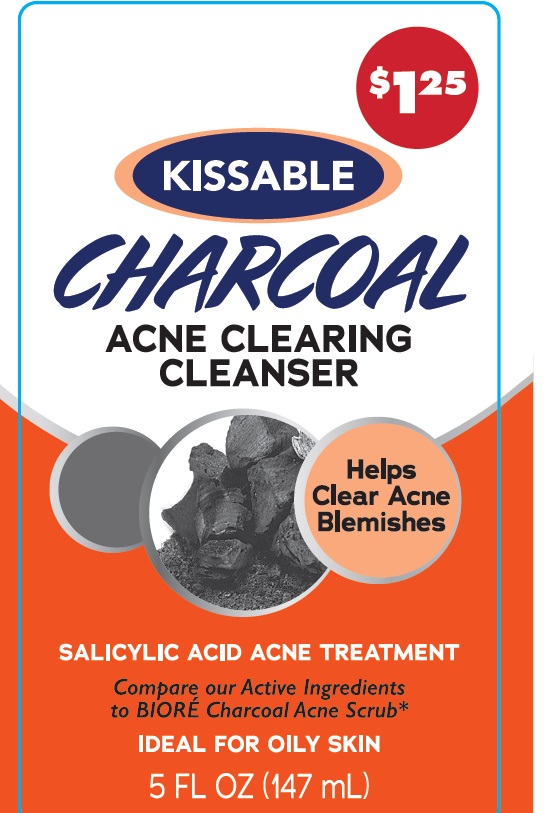 DRUG LABEL: Acne Cleanser
NDC: 50157-021 | Form: SOLUTION
Manufacturer: BRANDS INTERNATIONAL
Category: otc | Type: HUMAN OTC DRUG LABEL
Date: 20240510

ACTIVE INGREDIENTS: SALICYLIC ACID 1 mg/100 mL
INACTIVE INGREDIENTS: WATER; SODIUM LAURETH SULFATE; COCAMIDOPROPYL BETAINE; SODIUM LAURYL SULFATE; GLYCERIN; ALOE VERA LEAF; METHYLCHLOROISOTHIAZOLINONE; METHYLISOTHIAZOLINONE; HYDROXYMETHYL CELLULOSE; PROPYLENE GLYCOL; EDETATE SODIUM

Kissable Acne Wash Oil Free

Active Ingredient Purpose

Salicylic Acid 1% ............Acne Treatment

PURPOSE

for the treatment of Acne

INDICATIONS AND USAGE

clears up acne blemishes, blackheads and whiteheads

penetrates pores to control acne blemishes

helps prevent new acne blemishs from forming

Keep out of reach of children. If swallowed, get medical help or contact a Poison Control Center right away.

DOSAGE AND ADMINISTRATION

Wet face

Squeeze product into hands

massage over entire face

rinse thoroughly

for optimal results use up to 2-3 times per week

WARNINGS

Warning: for external use only. skin irritation and dryness is more likely to occur if you use another topical acne medication at the same time.

When using this product avoid contact with eyes. If contact occurs, flush thoroughly with water.

OTHER SAFETY INFORMATION

Store at room temparture

INACTIVE INGREDIENT

Inactive Ingredients:water, cocamidopropyl betaine, propylene glycol, sodium chloride, fragrance, Tetra sodium EDTA, aloe barbadensis leaf extract, methylchloroisothiazolinone, methylisothiazoline,